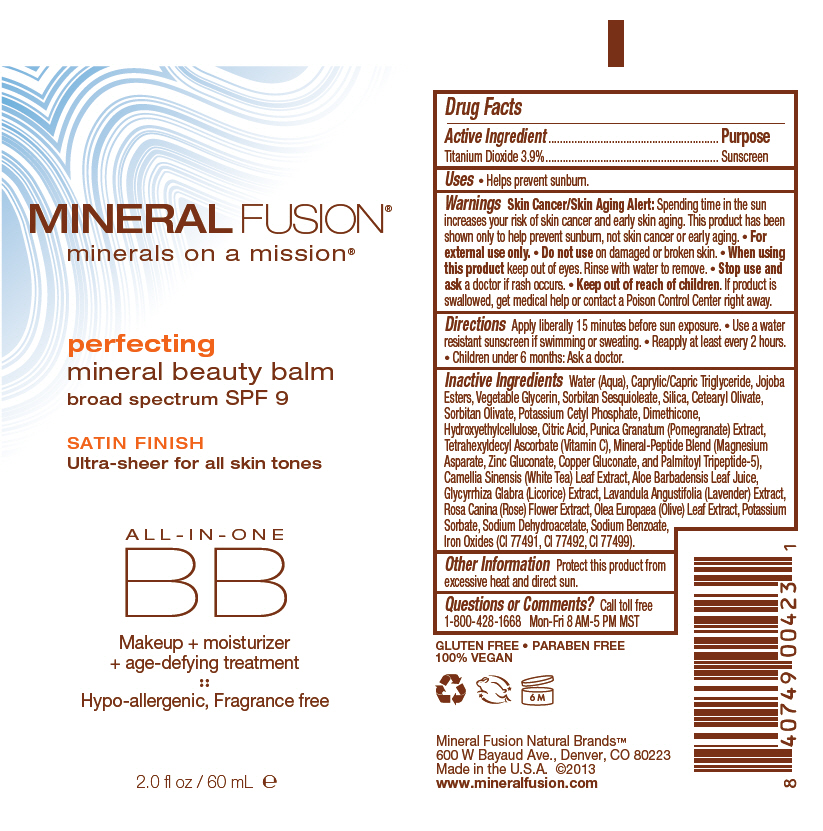 DRUG LABEL: Perfecting Mineral Beauty Balm with SPF 9
NDC: 55789-2400 | Form: CREAM
Manufacturer: Mineral Fusion Natural Brands LLC
Category: otc | Type: HUMAN OTC DRUG LABEL
Date: 20190918

ACTIVE INGREDIENTS: TITANIUM DIOXIDE 39 mg/1 mL
INACTIVE INGREDIENTS: WATER; MEDIUM-CHAIN TRIGLYCERIDES; JOJOBA OIL; GLYCERIN; SORBITAN SESQUIOLEATE; SILICON DIOXIDE; CETEARYL OLIVATE; SORBITAN OLIVATE; POTASSIUM CETYL PHOSPHATE; DIMETHICONE; HYDROXYETHYL CELLULOSE (100 MPA.S AT 2%); CITRIC ACID MONOHYDRATE; PUNICA GRANATUM ROOT BARK; TETRAHEXYLDECYL ASCORBATE; MAGNESIUM ASPARTATE; COPPER GLUCONATE; PALMITOYL TRIPEPTIDE-5; CAMELLIA SINENSIS FLOWER; ALOE VERA LEAF; GLYCYRRHIZA GLABRA; LAVANDULA ANGUSTIFOLIA SUBSP. ANGUSTIFOLIA FLOWERING TOP; ROSA CANINA FRUIT; OLEA EUROPAEA LEAF; POTASSIUM SORBATE; SODIUM DEHYDROACETATE; SODIUM BENZOATE; FERRIC OXIDE RED

Perfecting Mineral Beauty Balm with SPF 9

Drug Facts

Active Ingredient

Titanium Dioxide 3.9%

Purpose

Sunscreen

Uses

- Helps prevent sunburn.

Warnings

Skin Cancer/Skin Aging Alert

Spending time in the sun increases your risk of skin cancer and early skin aging. This product has been shown only to help prevent sunburn, not skin cancer or early aging.

- For external use only.

- Do not use on damaged or broken skin.

- When using this product keep out of eyes. Rinse with water to remove.

- Stop use and ask a doctor if rash occurs.

- Keep out of reach of children. If product is swallowed, get medical help or contact a Poison Control Center right away.

Directions

Apply liberally 15 minutes before sun exposure.

- Use a water resistant sunscreen if swimming or sweating.
- Reapply at least every 2 hours.
- Children under 6 months: Ask a doctor.

Inactive Ingredients

Water (Aqua), Caprylic/Capric Triglyceride, Jojoba Esters, Vegetable Glycerin, Sorbitan Sesquioleate, Silica, Cetearyl Olivate, Sorbitan Olivate, Potassium Cetyl Phosphate, Dimethicone, Hydroxyethylcellulose, Citric Acid, Punica Granatum (Pomegranate) Extract, Tetrahexyldecyl Ascorbate (Vitamin C), Mineral-Peptide Blend (Magnesium Asparate, Zinc Gluconate, Copper Gluconate, and Palmitoyl Tripeptide-5), Camellia Sinensis (White Tea) Leaf Extract, Aloe Barbadensis Leaf Juice, Glycyrrhiza Glabra (Licorice) Extract, Lavandula Angustifolia (Lavender) Extract, Rosa Canina (Rose) Flower Extract, Olea Europaea (Olive) Leaf Extract, Potassium Sorbate, Sodium Dehydroacetate, Sodium Benzoate, Iron Oxides (CI 77491, CI 77492, CI 77499).

Other Information

Protect this product from excessive heat and direct sun.

Questions or Comments?

Call toll free 1-800-428-1668 Mon-Fri 8 AM-5 PM MST

PRINCIPAL DISPLAY PANEL - 60 ml Tube Label

MINERAL FUSION®
minerals on a mission®

perfecting
mineral beauty balm
broad spectrum SPF 9

SATIN FINISH
Ultra-sheer for all skin tones

ALL-IN-ONE
BB

Makeup + moisturizer
+ age-defying treatment

Hypo-allergenic, Fragrance free

2.0 fl oz / 60 mL e